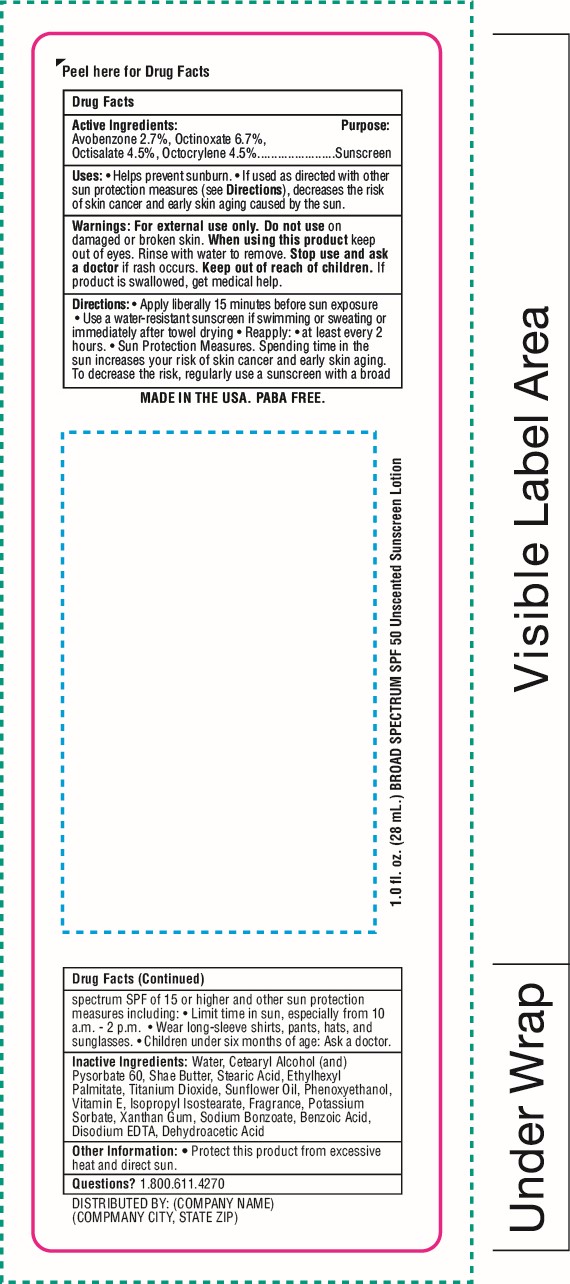 DRUG LABEL: SnugZ SPF 50 Broad Spectrum Sunscreen
NDC: 76309-551 | Form: LOTION
Manufacturer: SnugZ/USA, LLC
Category: otc | Type: HUMAN OTC DRUG LABEL
Date: 20251229

ACTIVE INGREDIENTS: OCTOCRYLENE 4.5 g/100 mL; AVOBENZONE 2.7 g/100 mL; OCTINOXATE 6.7 g/100 mL; OCTISALATE 4.5 g/100 mL
INACTIVE INGREDIENTS: WATER; SHEA BUTTER; SUNFLOWER OIL; .ALPHA.-TOCOPHEROL ACETATE; ISOPROPYL ISOSTEARATE; ETHYLHEXYL PALMITATE; STEARIC ACID; TITANIUM DIOXIDE; COCONUT OIL

SPF 50 Broad Spectrum Sunscreen Lotion